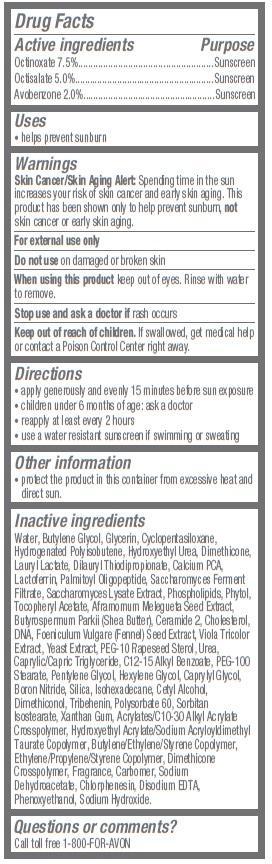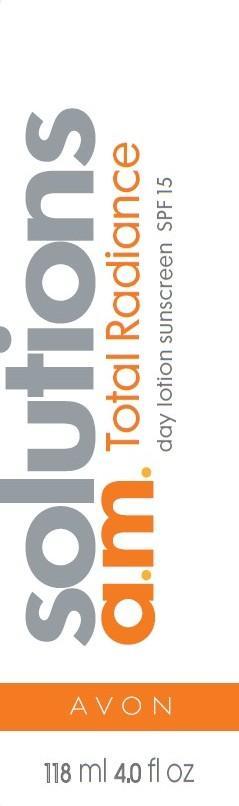 DRUG LABEL: Solutions
NDC: 10096-0168 | Form: LOTION
Manufacturer: Avon Products, Inc
Category: otc | Type: HUMAN OTC DRUG LABEL
Date: 20130208

ACTIVE INGREDIENTS: OCTINOXATE 75 mg/1 mL; OCTISALATE 50 mg/1 mL; AVOBENZONE 20 mg/1 mL

Active ingredients
Octinoxate 7.5%.......................................
Octisalate 5.0%........................................
Avobenzone 2.0%....................................

Purpose
.........................Sunscreen
......................Sunscreen
......................Sunscreen

Uses
• helps prevent sunburn

Warnings
Skin Cancer/Skin Aging Alert: Spending time in the sun increases your risk of skin cancer and early skin aging. This product has been shown only to help prevent sunburn, not skin cancer or early skin aging.
For external use only

Do not use on damaged or broken skin

When using this product keep out of eyes. Rinse with water to remove.

Stop use and ask a doctor if rash occurs

Keep out of reach of children. If swallowed, get medical help or contact a Poison Control Center right away.

Directions
• apply generously and evenly 15 minutes before sun exposure
• children under 6 months of age: ask a doctor
• reapply at least every 2 hours
• use a water resistant sunscreen if swimming or sweating

Other information
• protect the product in this container from excessive heat and direct sun.

Inactive ingredients
Water, Butylene Glycol, Glycerin, Cyclopentasiloxane, Hydrogenated Polyisobutene, Hydroxyethyl Urea, Dimethicone, Lauryl Lactate, Dilauryl Thiodipropionate, Calcium PCA, Lactoferrin, Palmitoyl Oligopeptide, Saccharomyces Ferment Filtrate, Saccharomyces Lysate Extract, Phospholipids, Phytol, Tocopheryl Acetate, Aframomum Melegueta Seed Extract, Butyrospermum Parkii (Shea Butter), Ceramide 2, Cholesterol, DNA, Foeniculum Vulgare (Fennel) Seed Extract, Viola Tricolor Extract, Yeast Extract, PEG-10 Rapeseed Sterol, Urea, Caprylic/Capric Triglyceride, C12-15 Alkyl Benzoate, PEG-100 Stearate, Pentylene Glycol, Hexylene Glycol, Caprylyl Glycol, Boron Nitride, Silica, Isohexadecane, Cetyl Alcohol, Dimethiconol, Tribehenin, Polysorbate 60, Sorbitan Isostearate, Xanthan Gum, Acrylates/C10-30 Alkyl Acrylate Crosspolymer, Hydroxyethyl Acrylate/Sodium Acryloyldimethyl Taurate Copolymer, Butylene/Ethylene/Styrene Copolymer, Ethylene/Propylene/Styrene Copolymer, Dimethicone Crosspolymer, Fragrance, Carbomer, Sodium Dehydroacetate, Chlorphenesin, Disodium EDTA, Phenoxyethanol, Sodium Hydroxide.

Questions or comments?
Call toll free 1-800-FOR-AVON